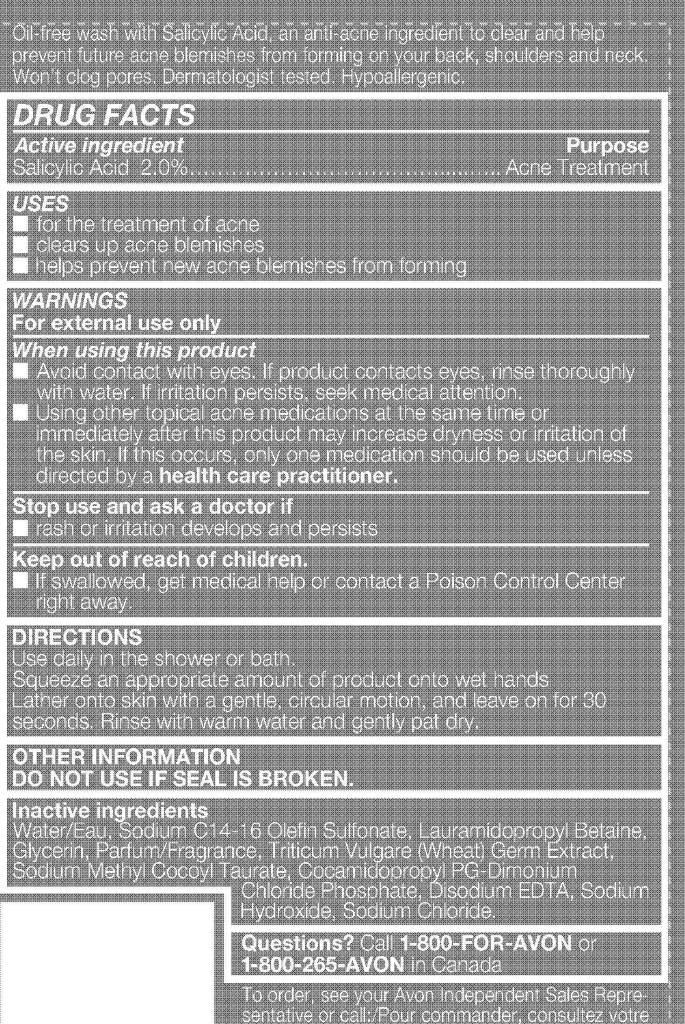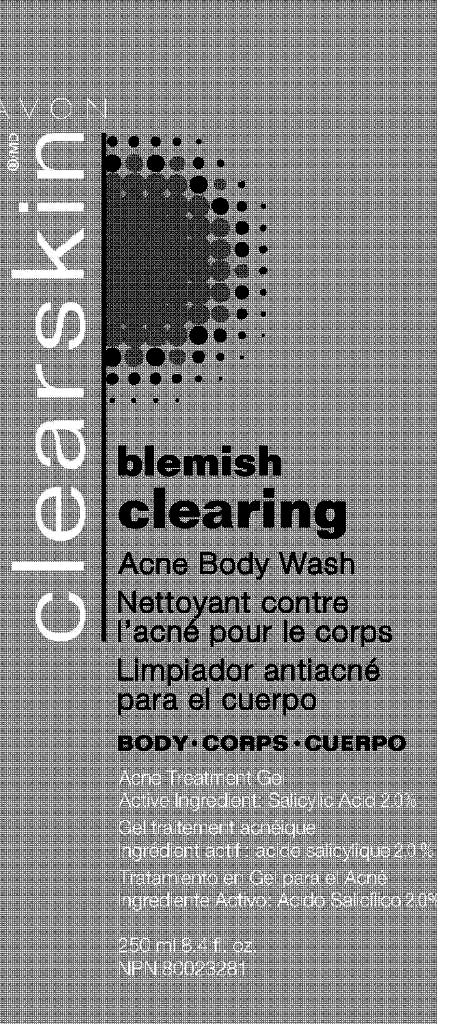 DRUG LABEL: Clearskin
NDC: 10096-0250 | Form: GEL
Manufacturer: New Avon LLC
Category: otc | Type: HUMAN OTC DRUG LABEL
Date: 20160212

ACTIVE INGREDIENTS: SALICYLIC ACID	 20 mg/1 mL

Active ingredient
Salicylic Acid 2.0%…………………

Purpose
………….....….. Acne Treatment

USES

- for the treatment of acne
- clears up acne blemishes
- helps prevent new acne blemishes from forming

WARNINGS
For external use only

When using this product

- Avoid contact with eyes. If product contacts eyes, rinse thoroughly with water. If irritation persists, seek medical attention.
- Using other topical acne medications at the same time or immediately after this product may increase dryness or irritation of the skin. If this occurs, only one medication should be used unless directed by a health care practitioner.

Stop use and ask a doctor if

- rash or irritation develops and persists

Keep out of reach of children.

- If swallowed, get medical help or contact a Poison Control Center right away.

DIRECTIONS
Use daily in the shower or bath.
Squeeze an appropriate amount of product onto wet hands
Lather onto skin with a gentle, circular motion, and leave on for 30
seconds. Rinse with warm water and gently pat dry.

OTHER INFORMATION
DO NOT USE IF SEAL IS BROKEN.

Inactive ingredients
Water/Eau, Sodium C14-16 Olefin Sulfonate, Lauramidopropyl Betaine,
Glycerin, Parfum/Fragrance, Triticum Vulgare (Wheat) Germ Extract,
Sodium Methyl Cocoyl Taurate, Cocamidopropyl PG-Dimonium
Chloride Phosphate, Disodium EDTA, Sodium
Hydroxide, Sodium Chloride.

Questions? Call 1-800-FOR-AVON or
1-800-265-AVON in Canada